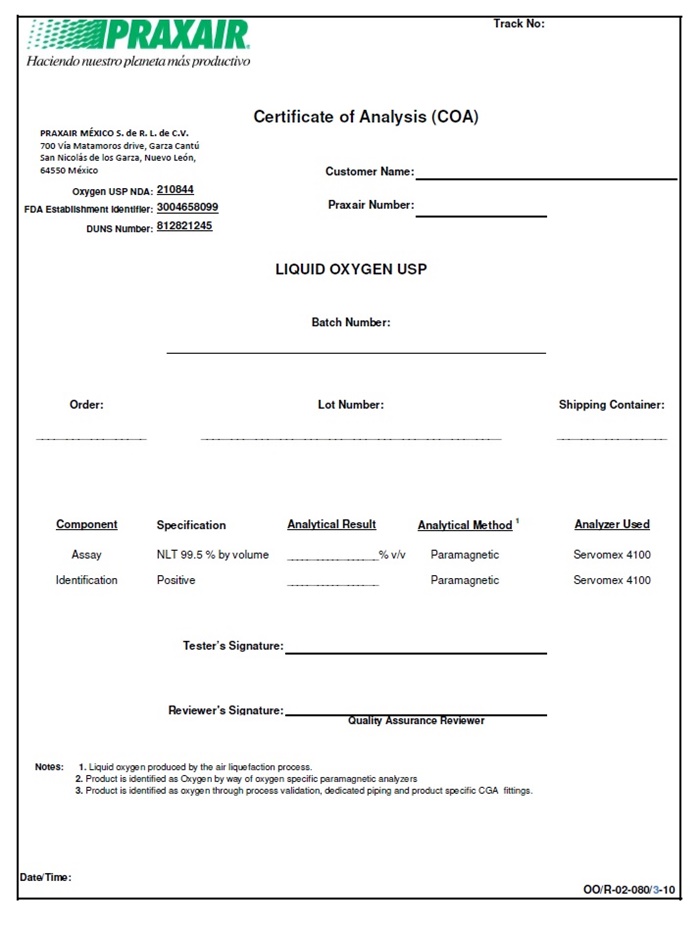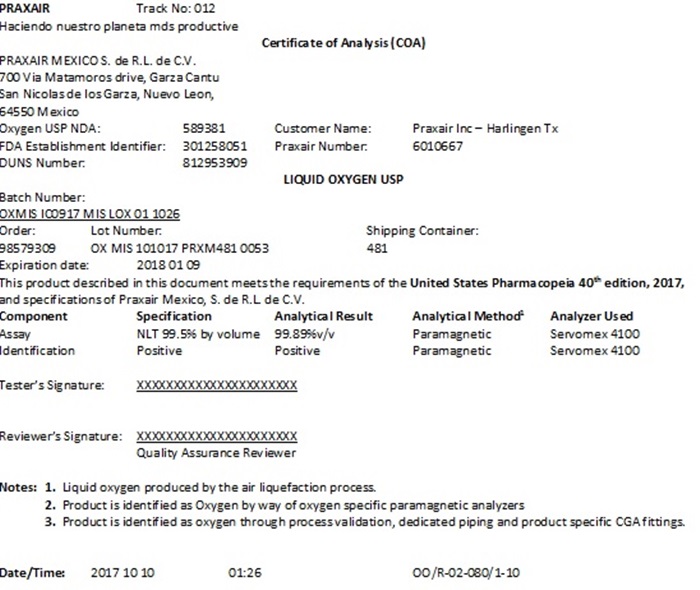 DRUG LABEL: OXYGEN
NDC: 72223-002 | Form: GAS
Manufacturer: Praxair Mexico, S. de R.L. de C.V
Category: prescription | Type: HUMAN PRESCRIPTION DRUG LABEL
Date: 20211109

ACTIVE INGREDIENTS: OXYGEN 990 mL/1 L

Oxygen

PACKAGE LABEL

PRAXAIR Track No: 012

Haciendo nuestro planeta mds productive

Certificate of Analysis (COA)

PRAXAIR MEXICO S. de R.L. de C.V.

700 Via Matamoros drive, Garza Cantu

San Nicolas de los Garza, Nuevo Leon,

64550 Mexico

Oxygen USP NDA: 589381 Customer Name: Praxair Inc – Harlingen Tx

FDA Establishment Identifier: 301258051 Praxair Number: 6010667

DUNS Number: 812953909

LIQUID OXYGEN USP

Batch Number:

OXMIS IC0917 MIS LOX 01 1026

Order: Lot Number: Shipping Container:

98579309 OX MIS 101017 PRXM481 0053 481

Expiration date: 2018 01 09

This product described in this document meets the requirements of the United States Pharmacopeia 40th edition, 2017, and specifications of Praxair Mexico, S. de R.L. de C.V.

Component Specification Analytical Result Analytical Method^1 Analyzer Used

Assay NLT 99.5% by volume 99.89%v/v Paramagnetic Servomex 4100

Identification Positive Positive Paramagnetic Servomex 4100

Tester’s Signature: XXXXXXXXXXXXXXXXXXXXXX

Reviewer’s Signature: XXXXXXXXXXXXXXXXXXXXXX

Quality Assurance Reviewer

Notes:1. Liquid oxygen produced by the air liquefaction process.

2. Product is identified as Oxygen by way of oxygen specific paramagnetic analyzers

3. Product is identified as oxygen through process validation, dedicated piping and product specific CGA fittings.

Date/Time: 2017 10 10 01:26 OO/R-02-080/1-10

PACKAGE LABEL

PRAXAIR Track No:

Haciendo nuestro planeta mds productive

Certificate of Analysis (COA)

PRAXAIR MEXICO S. de R.L. de C.V.

700 Via Matamoros drive, Garza Cantu

San Nicolas de los Garza, Nuevo Leon,

64550 Mexico

Oxygen USP NDA: 210844 Customer Name:

FDA Establishment Identifier: 3004658099 Praxair Number:

DUNS Number: 812821245

LIQUID OXYGEN USP

Batch Number: _________

Order: ________ Lot Number: __________ Shipping Container: ___________

Component Specification Analytical Result Analytical Method^1 Analyzer Used

Assay NLT 99.5% by volume _____%v/v Paramagnetic Servomex 4100

Identification Positive _________ Paramagnetic Servomex 4100

Tester’s Signature: __________________________

Reviewer’s Signature: _________________________

Quality Assurance Reviewer

Notes:1. Liquid oxygen produced by the air liquefaction process.

2. Product is identified as Oxygen by way of oxygen specific paramagnetic analyzers

3. Product is identified as oxygen through process validation, dedicated piping and product specific CGA fittings.

Date/Time: _______________________ OO/R-02-080/3-10